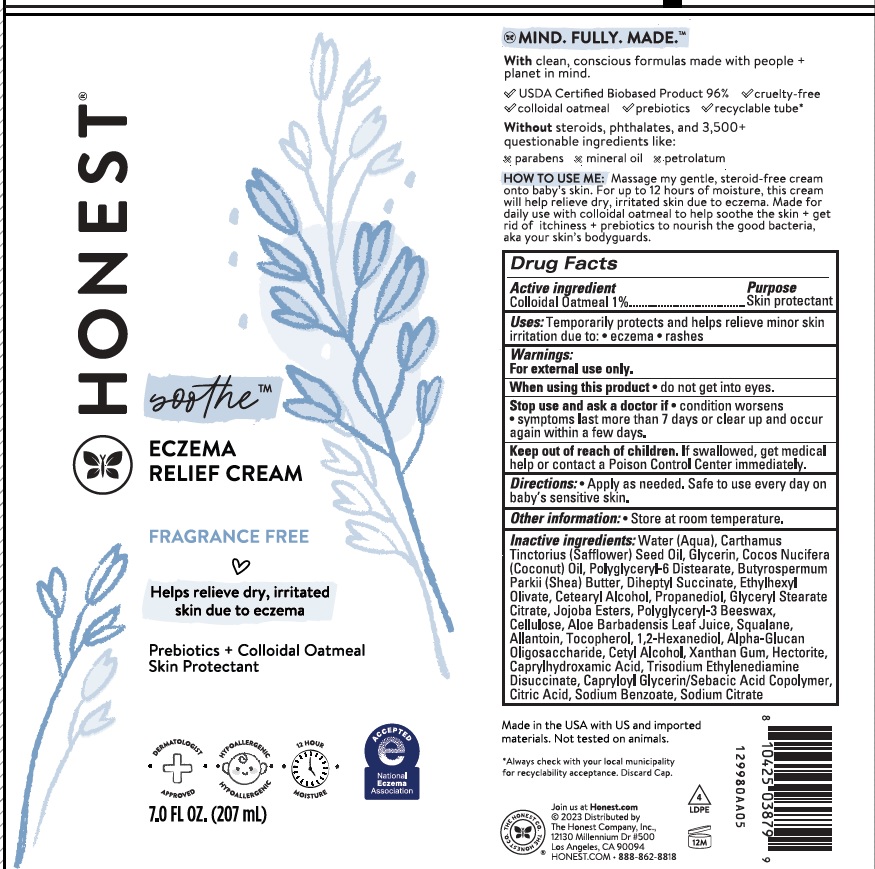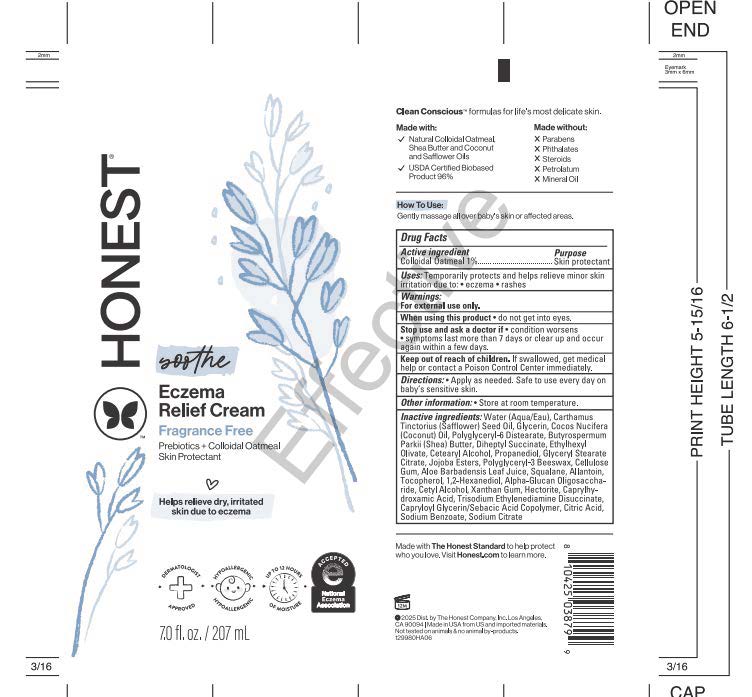 DRUG LABEL: Honest Eczema Cream
NDC: 69366-504 | Form: CREAM
Manufacturer: The Honest Company, Inc.
Category: otc | Type: HUMAN OTC DRUG LABEL
Date: 20251223

ACTIVE INGREDIENTS: OATMEAL 1 g/100 g
INACTIVE INGREDIENTS: POWDERED CELLULOSE; WATER; SAFFLOWER OIL; GLYCERIN; COCONUT OIL; POLYGLYCERYL-6 DISTEARATE; SHEA BUTTER; DIHEPTYL SUCCINATE; CETEARYL ALCOHOL; PROPANEDIOL; GLYCERYL STEARATE CITRATE; ALOE VERA LEAF; SQUALANE; ALLANTOIN; TOCOPHEROL; 1,2-HEXANEDIOL; .ALPHA.-GLUCAN OLIGOSACCHARIDE; CETYL ALCOHOL; XANTHAN GUM; HECTORITE; CAPRYLHYDROXAMIC ACID; TRISODIUM ETHYLENEDIAMINE DISUCCINATE; CAPRYLOYL GLYCERIN/SEBACIC ACID COPOLYMER (2000 MPA.S); CITRIC ACID MONOHYDRATE; SODIUM BENZOATE; SODIUM CITRATE, UNSPECIFIED FORM

Eczema Relief Cream

Active ingredient

Colloidal Oatmeal 1%

Purpose

Skin protectant

Uses:

Temporarily protects and helps relieve minor skin irritation due to:

- eczema
- rashes

Warnings:

For external use only.

When using this product

- do not get into eyes.

Stop use and ask a doctor if

- condition worsens
- symptoms last more than 7 days or clear up and occur again within a few days.

Keep out of reach of children.

If swallowed, get medical help or contact a Poison Control Center immediately.

Directions:

- Apply as needed. Safe to use every day on baby’s sensitive skin.

Other information:

- Store at room temperature.

Inactive ingredients:

Water (Aqua), Carthamus Tinctorius (Safflower) Seed Oil, Glycerin, Cocos Nucifera (Coconut) Oil, Polyglyceryl-6 Distearate, Butyrospermum Parkii (Shea) Butter, Diheptyl Succinate, Ethylhexyl Olivate, Cetearyl Alcohol, Propanediol, Glyceryl Stearate Citrate, Jojoba Esters, Polyglyceryl-3 Beeswax, Cellulose, Aloe Barbadensis Leaf Juice, Squalane, Allantoin, Tocopherol, 1,2-Hexanediol, Alpha-Glucan Oligosaccharide, Cetyl Alcohol, Xanthan Gum, Hectorite, Caprylhydroxamic Acid, Trisodium Ethylenediamine Disuccinate, Capryloyl Glycerin/Sebacic Acid Copolymer, Citric Acid, Sodium Benzoate, Sodium Citrate

Package/Label Principal Display Panel

HONEST®

soothe™

ECZEMA RELIEF CREAM

FRAGRANCE FREE

Helps relieve dry, irritated skin due to eczema

Prebiotics + Colloidal Oatmeal

Skin Protectant

7.0 FL. OZ. (207 mL)

HOW TO USE ME: Massage my gentle, steroid-free cream onto baby's skin. For up to 12 hours of moisture, this cream will help relieve dry, irritated skin due to eczema. Made for daily use with colloidal oatmeal to help soothe the skin + get rid of itchiness + prebiotics to nourish the good bacteria, aka your skin's bodyguards.

Made in the USA with US and imported materials.

©2023 Distributed by
The Honest Company, Inc.
12130 Millennium Dr #500
Los Angeles, CA 90094

HONEST.COM•call 888-862-8818

PACKAGE LABEL

HONEST ®

soothe™

ECZEMA RELIEF CREAM

FRAGRANCE FREE

Helps relieve dry, irritated skin due to eczema

Prebiotics + Colloidal Oatmeal

Skin Protectant

7.0 FL. OZ. (207 mL)

HOW TO USE ME: Massage my gentle, steroid-free cream onto baby's skin. For up to 12 hours of moisture, this cream will help relieve dry, irritated skin due to eczema. Made for daily use with colloidal oatmeal to help soothe the skin + get rid of itchiness + prebiotics to nourish the good bacteria, aka your skin's bodyguards.

Made in the USA with US and imported materials.

©2025 Distributed by
The Honest Company, Inc.
12130 Millennium Dr #500
Los Angeles, CA 90094

HONEST.COM